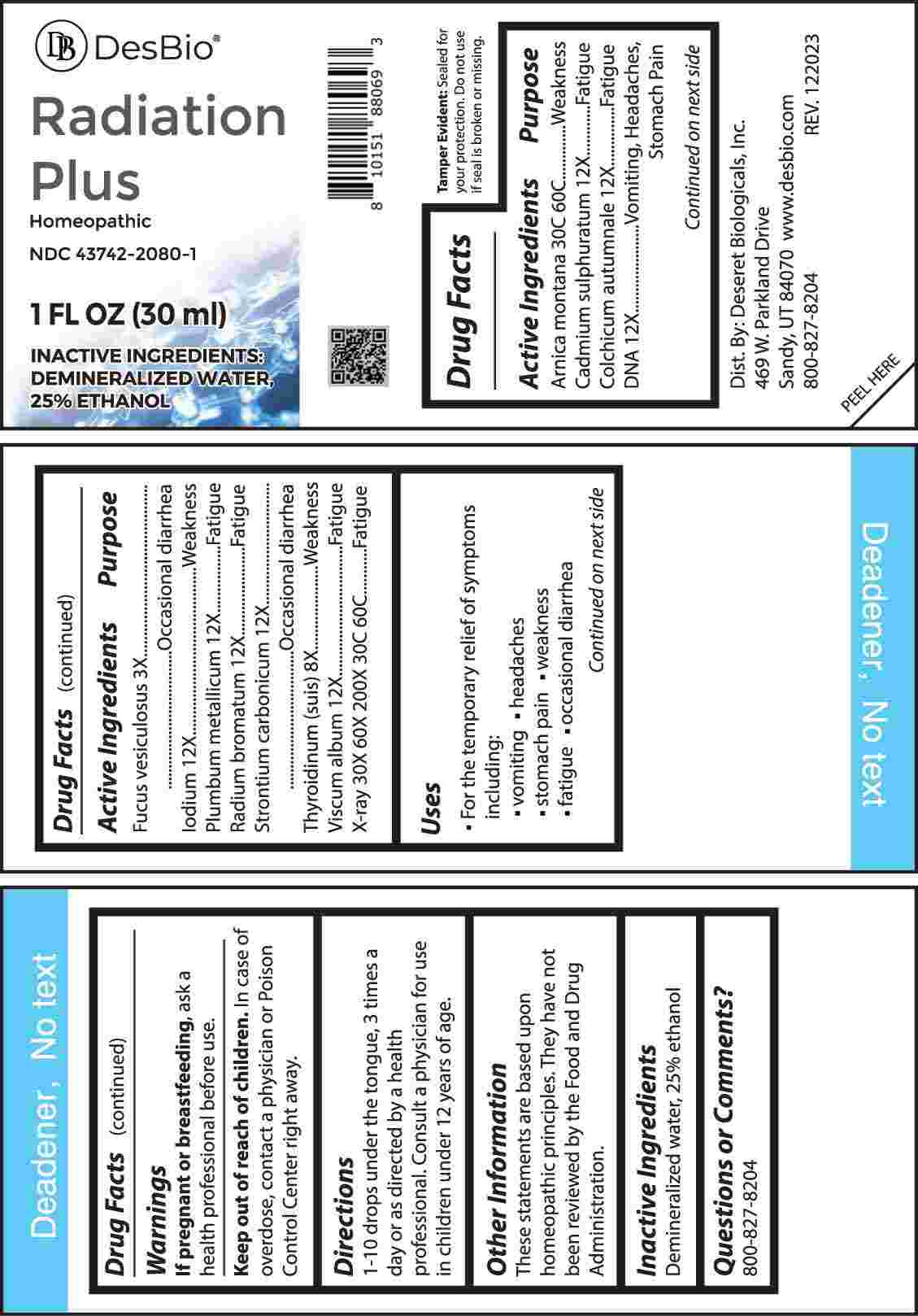 DRUG LABEL: Radiation Plus
NDC: 43742-2080 | Form: LIQUID
Manufacturer: Deseret Biologicals, Inc.
Category: homeopathic | Type: HUMAN OTC DRUG LABEL
Date: 20240423

ACTIVE INGREDIENTS: FUCUS VESICULOSUS 3 [hp_X]/1 mL; THYROID 8 [hp_X]/1 mL; CADMIUM SULFIDE 12 [hp_X]/1 mL; COLCHICUM AUTUMNALE BULB 12 [hp_X]/1 mL; HERRING SPERM DNA 12 [hp_X]/1 mL; IODINE 12 [hp_X]/1 mL; LEAD 12 [hp_X]/1 mL; RADIUM BROMIDE 12 [hp_X]/1 mL; STRONTIUM CARBONATE 12 [hp_X]/1 mL; VISCUM ALBUM FRUITING TOP 12 [hp_X]/1 mL; ALCOHOL, X-RAY EXPOSED (1000 RAD) 30 [hp_X]/1 mL; ARNICA MONTANA WHOLE 30 [hp_C]/1 mL
INACTIVE INGREDIENTS: WATER; ALCOHOL

DRUG FACTS:

ACTIVE INGREDIENTS:

Arnica Montana 30C, 60C, Cadmium Sulphuratum 12X, Colchicum Autumnale 12X, DNA 12X, Fucus Vesiculosus 3X, Iodium 12X, Plumbum Metallicum 12X, Radium Bromatum 12X, Strontium Carbonicum 12X, Thyroidinum (Suis) 8X, Viscum Album 12X, X-Ray 30X, 60X, 200X, 30C, 60C.

PURPOSE:

Arnica Montana - Weakness, Cadmium Sulphuratum - Fatigue, Colchicum Autumnale - Fatigue, DNA – Vomiting, Headaches, Stomach Pain, Fucus Vesiculosus – Occasional Diarrhea, Iodium - Weakness, Plumbum Metallicum - Fatigue, Radium Bromatum - Fatigue, Strontium Carbonicum – Occasional Diarrhea, Thyroidinum (Suis) - Weakness, Viscum Album - Fatigue, X-Ray - Fatigue

USES:

• For the temporary relief of symptoms including:

• vomiting • headaches • stomach pain • weakness • fatigue • occasional diarrhea

These statements are based upon homeopathic principles. They have not been reviewed by the Food and Drug Administration.

WARNINGS:

If pregnant or breast-feeding, ask a health professional before use.

Keep out of reach of children. In case of overdose, contact a physician or Poison Control Center right away.

Tamper Evident: Sealed for your protection. Do not use if seal is broken or missing.

KEEP OUT OF REACH OF CHILDREN:

In case of overdose, contact a physician or Poison Control Center right away.

DIRECTIONS:

1-10 drops under the tongue, 3 times a day or as directed by a health professional. Consult a physician for use in children under 12 years of age.

INACTIVE INGREDIENTS:

Demineralized water, 25% ethanol

QUESTIONS:

Dist. By: Deseret Biologicals, Inc.
469 W. Parkland Drive
Sandy, UT 84070

www.desbio.com

800-827-8204

PACKAGE LABEL DISPLAY:

DesBio

Radiation Plus

Homeopathic
NDC 43742-2080-1
1 FL OZ (30 ml)